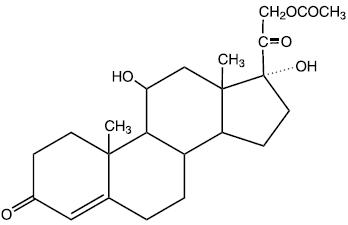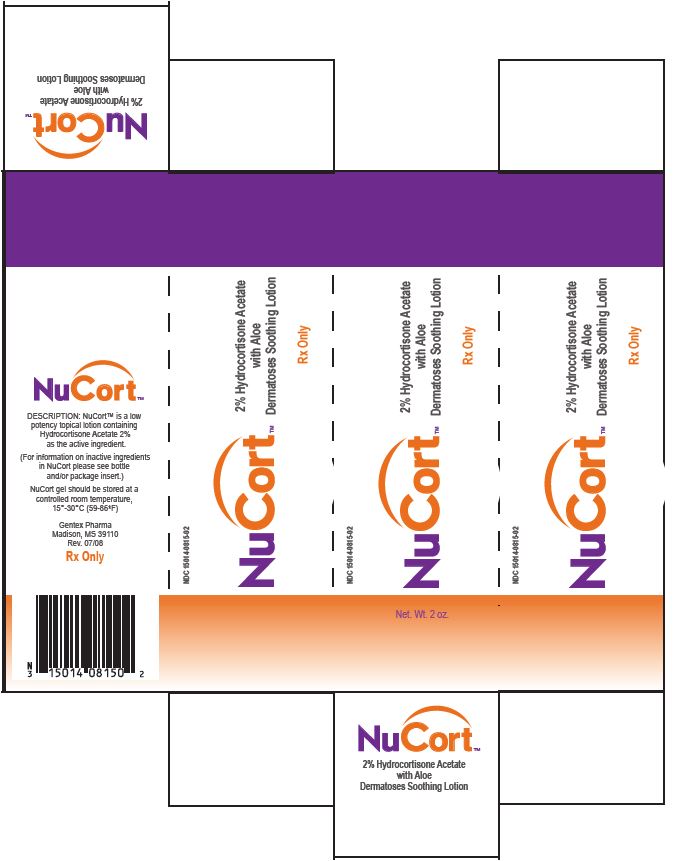 DRUG LABEL: NuCort
NDC: 15014-185 | Form: LOTION
Manufacturer: Gentex Pharma
Category: prescription | Type: HUMAN PRESCRIPTION DRUG LABEL
Date: 20130709

ACTIVE INGREDIENTS: HYDROCORTISONE ACETATE 20 mg/1 g
INACTIVE INGREDIENTS: CARBOMER HOMOPOLYMER TYPE C; ALOE VERA LEAF; BENZYL ALCOHOL ; ALKYL (C12-15) BENZOATE; CAMPHOR (SYNTHETIC); CETYL ALCOHOL; CETYL PALMITATE; DIMETHICONE; GLYCERIN; GLYCERYL MONOSTEARATE; MENTHOL; PEG-7 GLYCERYL COCOATE; POLYSORBATE 60; WATER; SORBITAN MONOSTEARATE; SQUALANE; TROLAMINE

NuCort lotion
(Hydrocortisone acetate 2%)

Rx Only

DESCRIPTION

DESCRIPTION: NuCort® (hydrocortisone acetate 2%) is a low potency topical lotion containing: Hydrocortisone Acetate 2% in a base containing: Acrylates/C10-30 Alkyl Acrylate Crosspolymer, Aloe Barbadensis Leaf Juice, Benzyl Alcohol, C12-15 Alkyl Bensoate, Camphor, Cetyl Alcohol, Cetyl Palmitate, Dimethicone, Glycerin, Glyceryl Stearate, Menthol, PEG-7 Glyceryl Cocoate, Polysorbate 60, Purified Water, Sorbitan Stearate, Squalane and Triethanolamine NuCort® contains a synthetic corticosteroid used as an anti-inflammatory Hydrocortisone acetate Molecular weight: 404.50. Solubility of hydrocortisone acetate in water: 1mg/100mL. Chemical name: Pregn-4-ene-3, 20-dione, 21-(acetyloxy)-11, 17-dihydroxy-(11β)-.The structural formula of hydrocortisone acetate is:

CLINICAL PHARMACOLOGY

CLINICAL PHARMACOLOGY: Topical corticosteroids share anti-inflammatory, antipruritic and vasoconstrictive actions. The mechanism of anti-inflammatory activity of the topical corticosteroids is unclear. Various laboratory methods, including vasoconstrictor assays, are used to compare and predict potencies and/or clinical efficacies of the topical corticosteroids. There is some evidence to suggest that a recognizable correlation exists between vasoconstrictor potency and therapeutic efficacy in man.

PHARMACOKINETICS

Pharmacokinetics: The extent of percutaneous absorption of topical corticosteroids is determined by many factors including the vehicle, the integrity of the epidermal barrier, and the use of occlusive dressings. Topical corticosteroids can be absorbed from normal intact skin. Inflammation and/or disease processes in the skin increase the percutaneous absorption of topical corticosteroids. Occlusive dressings substantially increase the percutaneous absorption of topical corticosteroids. Thus, occlusive dressings may be a valuable therapeutic adjunct for treatment of resistant dermatoses. (See DOSAGE AND ADMINISTRATION.)

Once absorbed through the skin, topical corticosteroids are handled through pharmacokinetic pathways similar to systemically administered corticosteroids. Corticosteroids are bound to plasma proteins in varying degrees. Corticosteroids are metabolized primarily in the liver and are then excreted by the kidneys. Some of the topical corticosteroids and their metabolites are also excreted into the bile.

INDICATIONS AND USAGE: NuCort lotion is a topical corticosteroid and is indicated for the relief of the inflammatory and pruritic manifestations of corticosteroid-responsive dermatoses.

CONTRAINDICATIONS

CONTRAINDICATIONS: Topical corticosteroid products are contraindicated in those patients with a history of hypersensitivity to any of the components of the preparation.

PRECAUTIONS:

GENERAL PRECAUTIONS

General: Systemic absorption of topical corticosteroids has produced reversible hypothalamicpituitary-adrenal (HPA) axis suppression, manifestations of Cushing’s syndrome, hyperglycemia and glucosuria in some patients. Conditions which augment systemic absorption include the application of the more potent steroids, use over large surface areas, prolonged use and the addition of occlusive dressings. Therefore, patients receiving a large dose of a potent topical steroid applied to a large surface area or under an occlusive dressing should be evaluated periodically for evidence of HPA axis suppression by using the urinary free cortisol and ACTH stimulation tests. If HPA axis suppression is noted, an attempt should be made to withdraw the drug, to reduce the frequency of application, or to substitute a less potent steroid. Recovery of HPA axis function is generally prompt and complete upon discontinuation of the drug. Infrequently, signs and symptoms of steroid withdrawal may occur, requiring supplemental systemic corticosteroids. In pediatric patients absorption may result in higher blood levels and thus more susceptibility to systemic toxicity. (See PRECAUTIONS-Pediatric Use.) If irritation develops, topical corticosteroids should be discontinued and appropriate therapy instituted.

In the presence of dermatological infections, the use of an appropriate antifungal or antibacterial agent should be instituted. If a favorable response does not occur promptly, the corticosteroid should be discontinued until the infection has been adequately controlled.

PATIENT COUNSELING INFORMATION

Information for the Patient: Patients using topical corticosteroids should receive the following information and instructions:

1. This medication is to be used as directed by the physician. It is for external use only. Avoid contact with the eyes.
2. Do not use this medication for any disorder other than for which it has been prescribed.
3. The treated skin area should not be bandaged or otherwise covered or wrapped as to be occlusive unless directed by the physician.
4. Report any signs of local adverse reactions especially under occlusive dressings.
5. Do not use any tight fitting diapers or plastic pants on a pediatric patient being treated in the diaper area, as these garments may constitute occlusive dressings.

LABORATORY TESTS

Laboratory Tests: The following tests may be helpful in evaluating the HPA axis suppression:

Urinary free cortisol test
ACTH stimulation test

CARCINOGENESIS AND MUTAGENESIS AND IMPAIRMENT OF FERTILITY

Carcinogenesis, Mutagenesis, and Impairment of Fertility: Long-term animal studies have not been performed to evaluate carcinogenic potential or the effect on fertility of topical corticosteroids.

PREGNANCY

Pregnancy Category C: Corticosteroids are generally teratogenic in laboratory animals when administered systemically at relatively low dosage levels. The more potent corticosteroids have been shown to be teratogenic after dermal application in laboratory animals. There are no adequate and well-controlled studies in pregnant women of teratogenic effects from topically applied corticosteroids. Therefore, topical corticosteroids should be used during pregnancy only if the potential benefit justifies the potential risk to the fetus. Drugs of this class should not be used extensively on pregnant patients, in large amounts, or for prolonged periods of time.

NURSING MOTHERS

Nursing mothers: It is not known whether topical administration of corticosteroids could result in sufficient systemic absorption to produce detectable quantities in breast milk. Systemically administered corticosteroids are secreted into breast milk in quantities not likely to have a deleterious effect on the infant. Caution should be exercised when any topical corticosteroids are administered to a nursing woman.

PEDIATRIC USE

Pediatric Use: Pediatric patients may demonstrate greater susceptibility to topical corticosteroid-Induced HPA axis suppression and Cushing’s Syndrome than mature patients because of a larger skin surface area to body weight ratio. Hypothalamic-pituitary-adrenal (HPA) axis suppression, Cushing’s syndrome and intracranial hypertension have been reported in pediatric patients receiving topical corticosteroids. Manifestations of adrenal suppression in pediatric patients include linear growth retardation, delayed weight gain, low plasma cortisone levels and absence of response to ACTH stimulation. Manifestations of intracranial hypertension include bulging fontanelles, headaches, and bilateral papilledema. Administration of topical corticosteroids to pediatric patients should be limited to the least amount compatible with an effective therapeutic regimen. Chronic corticosteroid therapy may interfere with the growth and development of pediatric patients.

GERIATRIC USE

Geriatric Use: Reported clinical experience has not identified differences in responses between the elderly and younger patients. In general, dose selection for an elderly patient should be cautious using the least amount compatible with an effective therapeutic regimen and reflecting the greater frequency of decreased hepatic, renal or cardiac function, and of concomitant disease or other drug therapy.

ADVERSE REACTIONS

ADVERSE REACTIONS: The following local adverse reactions are reported infrequently with topical corticosteroids, but may occur more frequently with the use of occlusive dressings. These reactions are listed in an approximately decreasing order of occurrence: Burning, Itching, Irritation, Dryness, Folliculitis, Hypertrichosis, Acneiform eruptions, Hypopigmentation, Perioral dermatitis, Allergic contact dermatitis, Maceration of the skin, Secondary infection, Skin atrophy, Striae, Miliaria

OVERDOSAGE

OVERDOSAGE: Topically applied corticosteroids can be absorbed in sufficient amounts to produce systemic effects. (See PRECAUTIONS.)

DOSAGE AND ADMINISTRATION: Apply to affected area 3 to 4 times daily. Occlusive dressings may be used for the management of psoriasis or recalcitrant conditions.

HOW SUPPLIED:

NuCort® is supplied in 2oz. bottles (NDC 15014-0185-01, NDC 15014-0185-02)

STORAGE AND HANDLING

Store upright at controlled room temperature 15° – 30°C (59° – 86°F).

Distributed by:
Gentex Pharma
Madison, MS 39110

Rev. 08/10

PRINCIPAL DISPLAY PANEL - 56.7 g

NDC 15014-0815-02

NuCort TM

2% Hydrocortisone Acetate
with Aloe
Dermatoses Soothing Lotion

Net Wt 2 oz

Rx Only

Gentex Pharma
Madison, MS 39110